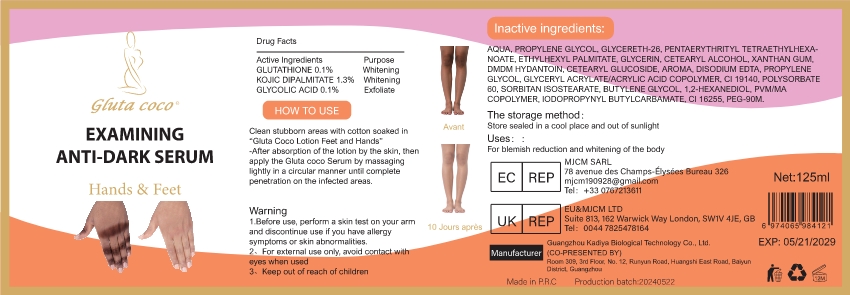 DRUG LABEL: EXAMINING ANTI-DARK SERUM
NDC: 84423-002 | Form: EMULSION
Manufacturer: Guangzhou Kadiya Biotechnology Co., Ltd.
Category: otc | Type: HUMAN OTC DRUG LABEL
Date: 20240612

ACTIVE INGREDIENTS: KOJIC DIPALMITATE 1.625 mg/125 mL
INACTIVE INGREDIENTS: ETHYLHEXYL PALMITATE; POLYSORBATE 60; PENTAERYTHRITYL TETRAETHYLHEXANOATE; XANTHAN GUM; PROPYLENE GLYCOL 1,2-DISTEARATE; GLYCERETH-26; WATER

active

KOJIC DIPALMITATE:1.3% Whitening

Inactive

Aqua :71%

PROPYLENE GLYCOL:15%

GLYCERETH-26:7%

Purpose

For blemish reduction and whitening of the body

Warining

Warning
1.Before use, perform a skin test on your arm and discontinue use if you have allergy symptoms or skin abnormalities.
2、For external use only, avoid contact with eyes when used
3、Keep out of reach of children

Not not use

For external use only, avoid contact witheyes when used ，Keep out of reach of children.

stop to use

Before use, perform a skin test on your arm and discontinue use if you have allergy symptoms or skin abnormalities

When

Clean stubborn areas with cotton soaked in“Gluta Coco Lotion Feet and Hands'

Out of Children

Keep out of reach of children

how to use

Clean stubborn areas with cotton soaked in*Gluta Coco Lotion Feet and Hands,-After absorption of the lotion by the skin, thenapply the Gluta coco Serum by massaginglightly in a circular manner until completepenetration on the infected areas.

Dosage

After absorption of the lotion by the skin, thenapply the Gluta coco Serum by massaginglightly in a circular manner until completepenetration on the infected areas.

Principlan display panel

EXAMININGANTI-DARK SERUM

Warning
1.Before use, perform a skin test on your arm
and discontinue use if you have allergy
symptoms or skin abnormalities.
2、For external use only, avoid contact with
eyes when used
3、Keep out of reach of children